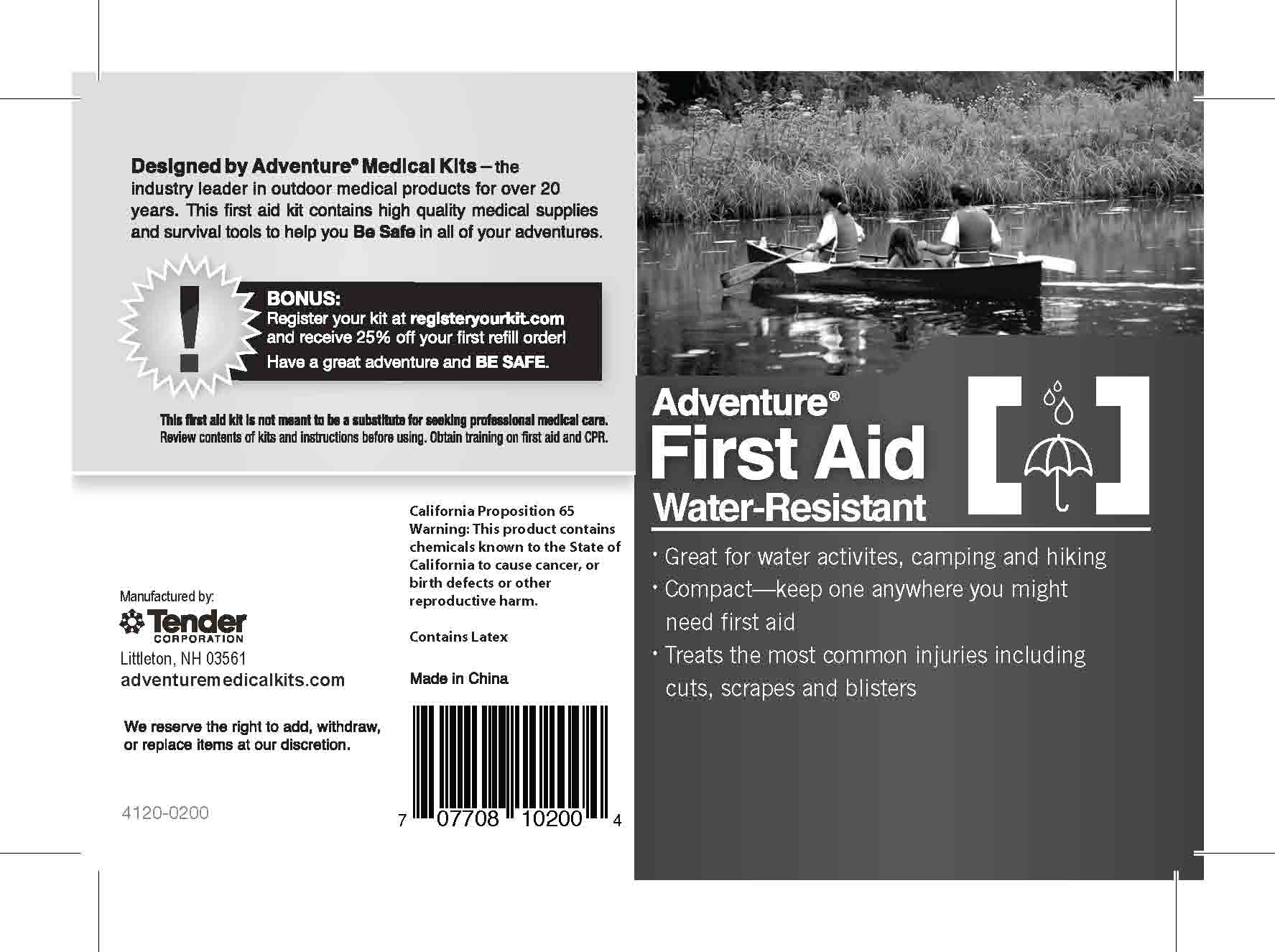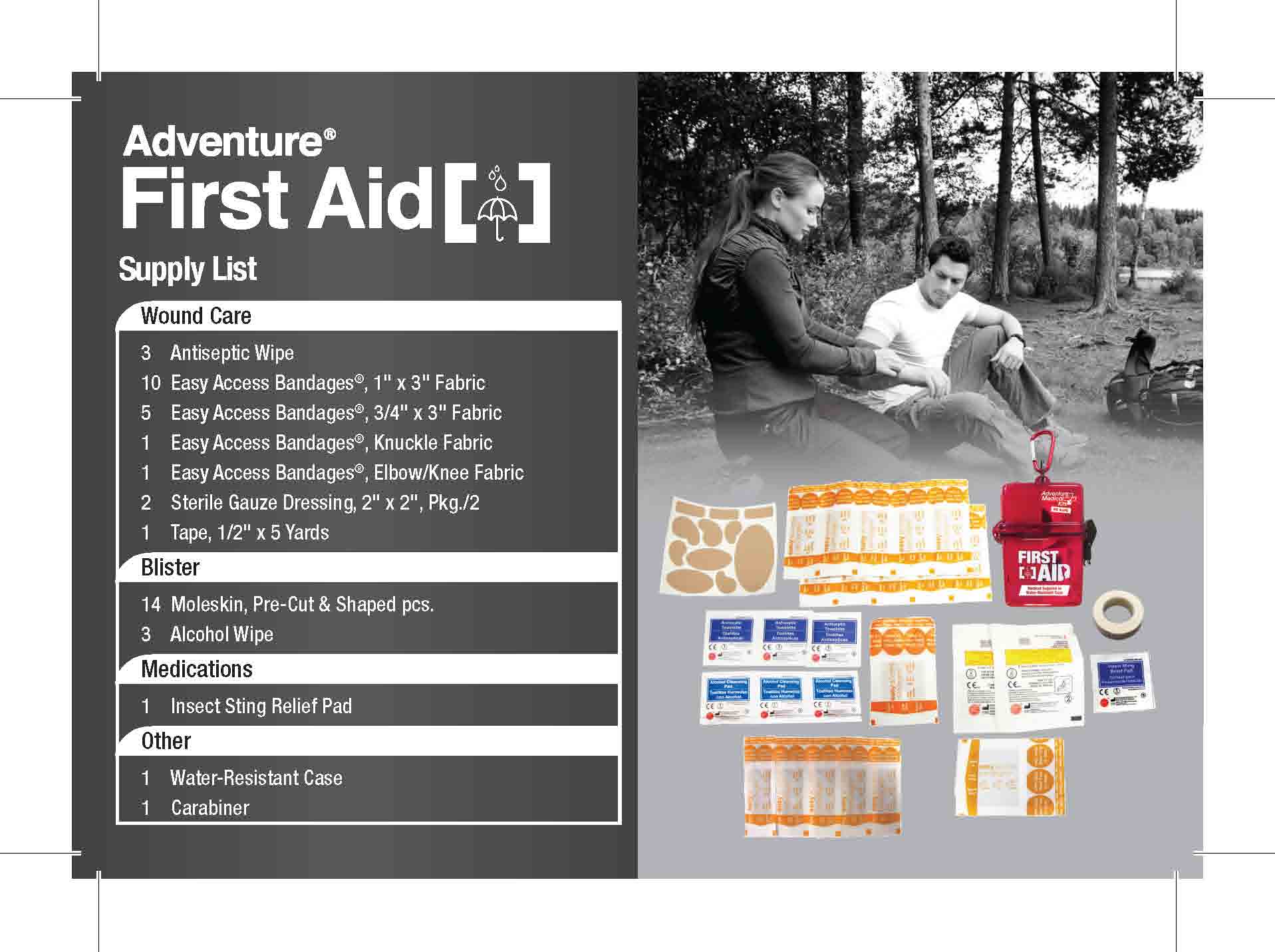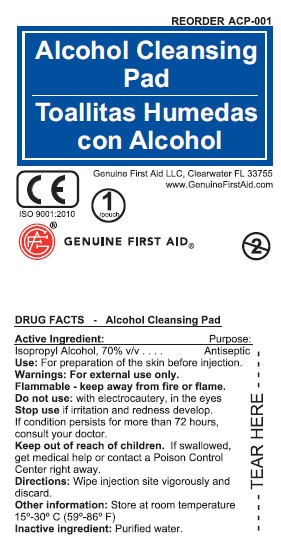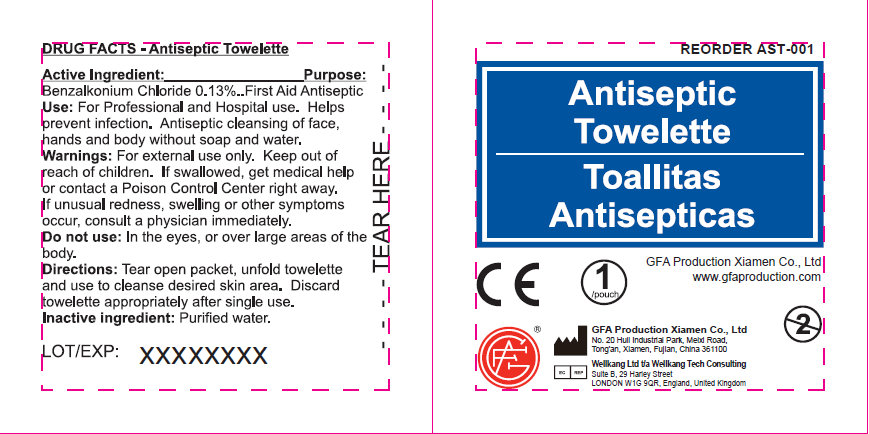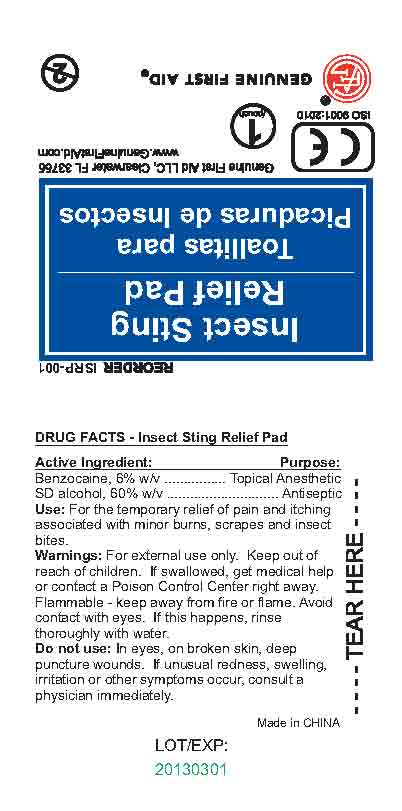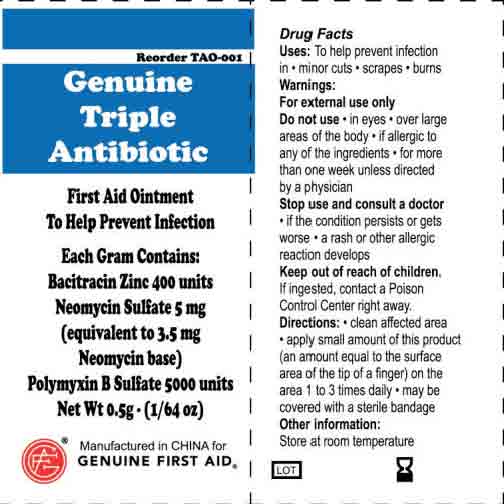 DRUG LABEL: Adventure First Aid .5 Tin
NDC: 44224-0203 | Form: KIT | Route: TOPICAL
Manufacturer: Tender Corporation
Category: otc | Type: HUMAN OTC DRUG LABEL
Date: 20170316

ACTIVE INGREDIENTS: BENZOCAINE 0.6 mg/100 mL; ALCOHOL 60 mL/100 mL; ISOPROPYL ALCOHOL 700 mg/1 mL; BENZALKONIUM CHLORIDE 1.3 mg/1 mL; NEOMYCIN SULFATE 5 mg/1 g; POLYMYXIN B SULFATE 5000 [iU]/1 g; BACITRACIN ZINC 400 [iU]/1 g
INACTIVE INGREDIENTS: WATER; WATER; WATER; PETROLATUM; WATER; MINERAL OIL

Adventure First Aid .5 Tin

Active Ingredient - Antiseptic

Benzalkonium Chloride 0.13%

Purpose - Antiseptic

Antiseptic

Use - Antiseptic

For Professional and hospital use. Helps prevent infection. Antiseptic cleansing of face, hands and body without soap and water.

Warnings, Precautions and Directions - Antiseptic

For External use only.

Keep out of Reach of Children.

Stop use if unusual redness, swelling or other symptoms occur, consult a physician immediately.

Do not uses in eyes or over large areas of the body.

Tear open packet, unfold towelette and use to cleanse desired skin area. Discard towelette appropriately after single use.

Inactive Ingredients - Antiseptic

Purified Water

Active Ingredient - Alcohol Prep Pad

Isopropyl Alcohol 70%

Use - Alcohol Prep Pad

For preparation of the skin before injection

Warnings, Precautions and Directions - Alcohol Prep Pad

For External Use Only

Flammable - Keep away from fire or flame

Do Not Use - with electrocautery, in eyes

Stop Use and Ask a Doctor if - Irritation or redness develop and persists for more than 72 hours

Keep out of Reach of Children

If swallowed, get medical help or contact a poison control center right away.

Tear Open packet, unfold and use as and wipe injection site vigorously and discard.

Store at Room Temperature

Active Ingredients - Insect Relief Pad

Benzocaine 6%

SD alcohol 60%

Purpose - Insect Relief Pad

Topical Anesthetic - Antiseptic

Use - Insect Relief Pad

For the temporary relief of pain and itching associated with minor burns, scrapes and insect bites

Warnings, Precautions and Directions - Insect Relief Pad

Clean intended area thoroughly with pad. Discard after single use

Warnings: For external use only.

Avoid contact with eyes. If this happens, rinse thoroughly with water

If swallowed, get medical help or contact a Poison Control Center right away

Flammable - keep away from fire or flame

Do not use: In eyes, on broken skin, deep puncture wounds. If unusual redness, swelling, irritation or other symptoms occur, consult a physician immediately.

Active Ingredients - Triple Antibiotic Ointment

Bacitracin Zinc 400 units

Neomycin Sulfate 5mg (equivalent to 3.5 mg Neomycin base)

Polymyxin B Sulfate 5000 units

Purpose - Triple Antibiotic Ointment

Triple Antibiotic

Use - Triple Antibiotic Ointment

To help prevent infection in: minor cuts; scrapes and burns

Warnings, Precautions and Directions - Triple Antibiotic Ointment

For external use only.

Do not use: in eyes; over large areas of the body;

If allergic to any of the ingredients; for more than one week unless directed by a physician

Stop use and consult a doctor: if the condition persists or gets worse; a rash or other allergic reaction develops.

Keep out of reach of children.

If ingested, contact a Poison Control Center right away

Directions: clean affected area; apply small amount of this product (an amount equal to the surface area of the tip of a finger) on the area 1 to 3 times daily; may be covered with a sterile bandage.